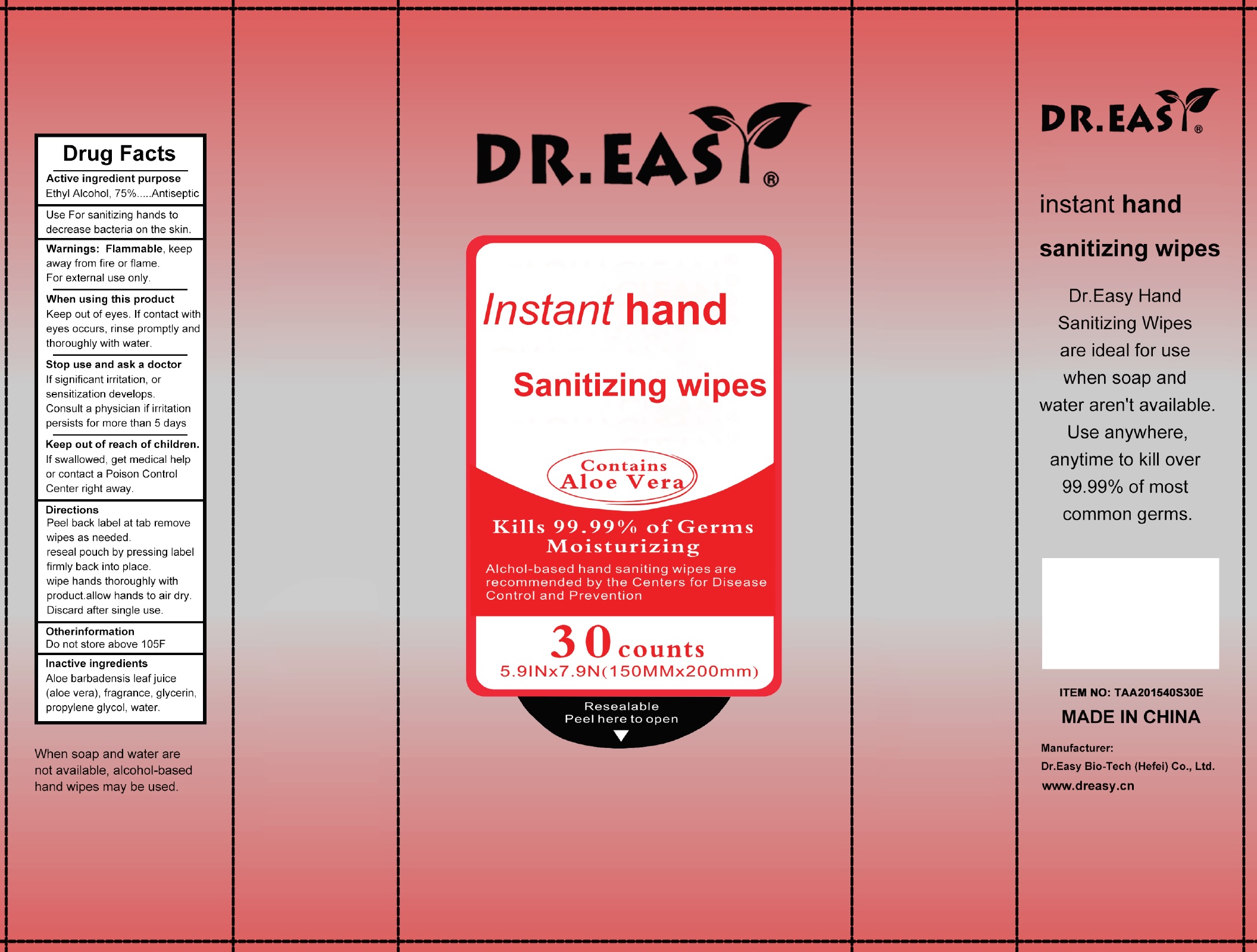 DRUG LABEL: Dr. Easy Instant Hand Sanitizing Wipes
NDC: 52056-000 | Form: CLOTH
Manufacturer: Dr. Easy Bio-Tech (Hefei) Co., Ltd.
Category: otc | Type: HUMAN OTC DRUG LABEL
Date: 20200902

ACTIVE INGREDIENTS: ALCOHOL 0.75 mL/1 mL
INACTIVE INGREDIENTS: ALOE VERA LEAF; GLYCERIN; PROPYLENE GLYCOL; WATER

Dr. Easy Instant Hand Sanitizing Wipes

Active ingredient

Ethyl Alcohol, 75%

purpose

Antiseptic

Use

For sanitizing hands to decrease bacteria on the skin.

Warnings:

Flammable, keep away from fire or flame. For external use only.

When using this product

Keep out of eyes. If contact with eyes occurs, rinse promptly and thoroughly with water.

Stop use and ask a doctor

If significant irritation, or sensitization develops. Consult a physician if irritation persists for more than 5 days

Keep out of reach of children.

If swallowed, get medical help or contact a Poison Control Center right away.

Directions

Peel back label at tab remove wipes as needed. reseal pouch by pressing label firmly back into place. wipe hands thoroughly with product.allow hands to air dry. Discard after single use.

Other information

Do not store above 105F

Inactive ingredients

Aloe barbadensis leaf juice (aloe vera), fragrance, glycerin, propylene glycol, water.